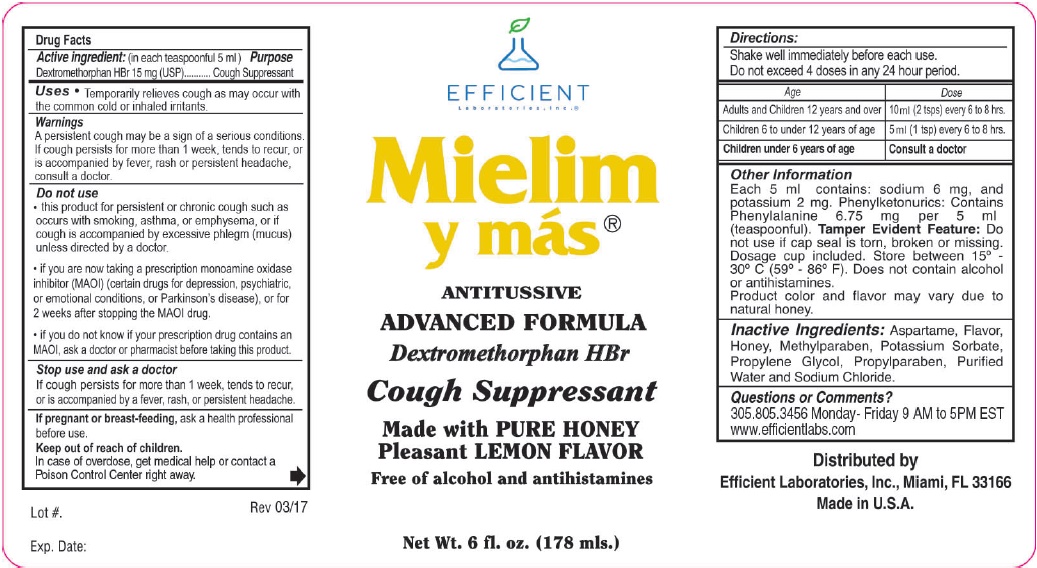 DRUG LABEL: Mielim y mas
NDC: 58593-295 | Form: LIQUID
Manufacturer: Efficient Laboratories Inc.
Category: otc | Type: HUMAN OTC DRUG LABEL
Date: 20241014

ACTIVE INGREDIENTS: DEXTROMETHORPHAN HYDROBROMIDE 15 mg/5 mL
INACTIVE INGREDIENTS: ASPARTAME; HONEY; POTASSIUM SORBATE; PROPYLENE GLYCOL; PROPYLPARABEN; METHYLPARABEN; WATER; SODIUM CHLORIDE

Drug Facts

Active Ingredient: (In each teaspoonful 5 mls) Purpose

Dextromethorphan HBr 15 mg (USP)................................................Cough Suppressant

PURPOSE

Cough Suppressant

Warnings

A persistent cough may be a sign of a serious condition. If cough persists for more than 1 week, tends to recur, or is accompanied by fever, rash or persistent headache, consult a doctor.

Do not use

- this product for persistent or chronic cough such as occurs with smoking, asthma, or emphysema, or if cough is accompanied by excessive phlegm (mucus) unless directed by a doctor.
- if you are now taking a prescription monoamine oxidase inhibitor
  (MAOI) (certain drugs for depression, psychiatric, or emotional
  conditions, or Parkinson’s disease), or for 2 weeks after stopping
  the MAOI drug.
- if you do not know if your prescription drug contains an MAOI,
  ask a doctor or pharmacist before taking this product.

Stop use and ask a doctor

- if cough persists for more than 1 week, tends to recur, or is accompanied by a fever, rash or persistent headache.

Keep Out of Reach of Children.

In case of accidental overdose, get medical help or contact the Poison Control Center right away.

PREGNANCY OR BREAST FEEDING

If pregnant or breast-feeding,ask a health professional before use.

Directions:

Shake well immediately before use.

Do not exceed 4 doses in any 24 hour period.

Adults and Children 12 years and over - 10 ml (2 tsps) every 6 to 8 hours
Children 6 to under 12 years of age - 5 ml (1 tsp) every 6 to 8 hours
Children under 6 years of age - Consult a doctor

INDICATIONS AND USAGE

Temporarily relieves cough as may occur with the common cold or inhaled irritants.

Inactive Ingredients: Aspartame, Flavor, Honey,
Methylparaben, Potassium Sorbate, Propylene
Glycol, Propylparaben, Purified Water and Sodium
Chloride.

Questions or Comments?

305.805.3456 Monday-Friday 9AM to 5PM EST

www.efficientlabs.com